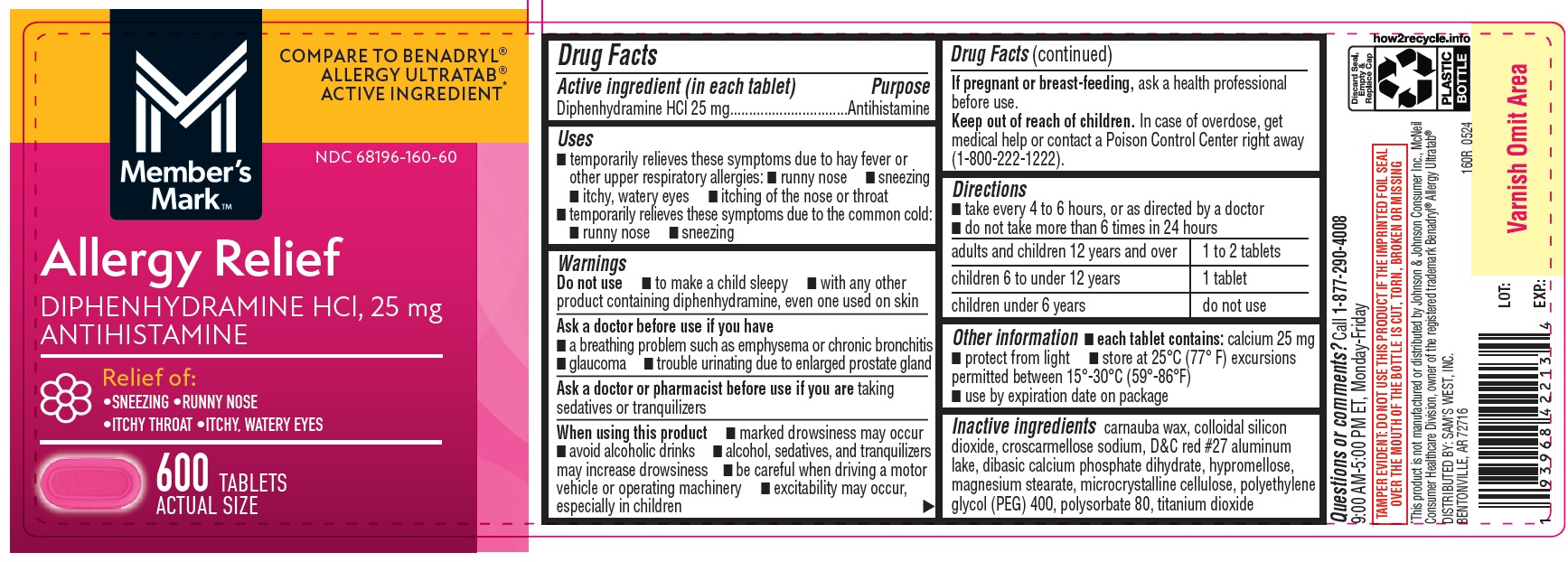 DRUG LABEL: Allergy Relief
NDC: 68196-160 | Form: TABLET
Manufacturer: SAM'S WEST INC
Category: otc | Type: HUMAN OTC DRUG LABEL
Date: 20251029

ACTIVE INGREDIENTS: DIPHENHYDRAMINE HYDROCHLORIDE 25 mg/1 1
INACTIVE INGREDIENTS: CROSCARMELLOSE SODIUM; TITANIUM DIOXIDE; CARNAUBA WAX; SILICON DIOXIDE; D&C RED NO. 27 ALUMINUM LAKE; DIBASIC CALCIUM PHOSPHATE DIHYDRATE; HYPROMELLOSES; MAGNESIUM STEARATE; MICROCRYSTALLINE CELLULOSE; POLYETHYLENE GLYCOL 400; POLYSORBATE 80

Sams Club Diphenhydramine Hydrochloride 25 mg Tablets

Active ingredients (in each tablet)

Diphenhydramine HCl 25 mg

Purpose

Antihistamine

Uses

temporarily relieves these symptoms due to hay fever or other upper respiratory allergies:

- runny nose
- sneezing
- itchy, watery eyes
- itching of the nose or throat

temporarily relieves these symptoms due to the common cold:

- runny nose
- sneezing

Warnings

Do not use

- to make a child sleepy
- with any other product containing diphenhydramine, even one used on skin

Ask a doctor before use if you have

- a breathing problem such as emphysema or chronic bronchitis
- glaucoma
- trouble urinating due to enlarged prostate gland

Ask a doctor or pharmacist before use if you aretaking sedatives or tranquilizers.

When using this product

- marked drowsiness may occur
- avoid alcoholic drinks
- alcohol, sedatives, and tranquilizers may increase drowsiness
- be careful when driving a motor vehicle or operating machinery
- excitability may occur, especially in children

PREGNANCY OR BREAST FEEDING

If pregnant or breast-feeding,ask a health professional before use.

Keep out of reach of children.In case of overdose, get medical help or contact a Poison Control Center right away (1-800-222-1222).

Directions

- take every 4 to 6 hours, or as directed by a doctor
- do not take more than 6 times in 24 hours

adults and children 12 years and over | 1 to 2 tablets
children 6 to under 12 years | 1 tablet
children under 6 years | do not use

Other information

- each tablet contains:calcium 25 mg
- protect from light
- store at 25°C (77° F) excursions permitted between 15°-30°C (59°-86°F)
- use by expiration date on package

INACTIVE INGREDIENT

Inactive ingredientscarnauba wax, colloidal silicon dioxide, croscarmellose sodium, D&C red #27 aluminum lake, dibasic calcium phosphate dihydrate, hypromellose, magnesium stearate, microcrystalline cellulose, polyethylene glycol (PEG) 400, polysorbate 80, titanium dioxide

Questions or comments?

Call 1-877-290-4008 9:00 AM-5:00 PM ET, Monday-Friday